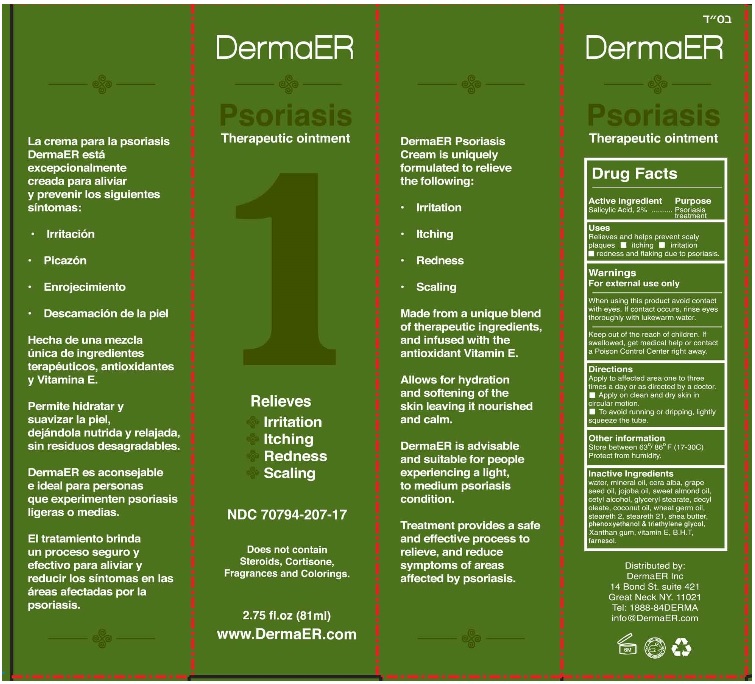 DRUG LABEL: DermaER Psoriasis Therapeutic
NDC: 70794-207 | Form: OINTMENT
Manufacturer: Chen Cohen Industries Inc.
Category: otc | Type: HUMAN OTC DRUG LABEL
Date: 20250527

ACTIVE INGREDIENTS: SALICYLIC ACID 20 mg/1 g
INACTIVE INGREDIENTS: WATER; MINERAL OIL; WHITE WAX; GRAPE SEED OIL; JOJOBA OIL; ALMOND OIL; CETYL ALCOHOL; GLYCERYL MONOSTEARATE; DECYL OLEATE; COCONUT OIL; WHEAT GERM OIL; STEARETH-2; STEARETH-21; SHEA BUTTER; PHENOXYETHANOL; TRIETHYLENE GLYCOL; XANTHAN GUM; .ALPHA.-TOCOPHEROL; BUTYLATED HYDROXYTOLUENE; FARNESOL

Drug Facts

Active Ingredient

Salicylic Acid....2%

Purpose

Psoriasis treatment

Uses

Relieves and helps prevent scaly plaques

- itching
- irritation
- redness and flaking due to psoriasis

Warnings

For external use only

When using this product

avoid contact with eyes. If contact occurs, rinse eyes thoroughly with lukewarm water.

Keep out of reach of children

If swallowed, get medical help or contact a Poison Control Center right away.

Directions

Apply to the affected area one to three times a day or as directed by a doctor.

- Apply on clean and dry skin in circular motion.
- To avoid running or dripping, lightly squeeze the tube.

Other information

Store between 63°/80°F (17-30C)

Protect from humidity.

Inactive Ingredients

water, mineral oil, cera alba, grape seed oil, jojoba oil, sweet almond oil, cetyl alcohol, glyceryl stearate, decyl oleate, coconut oil, wheat germ oil, steareth 2, steareth 21, shea butter, phenoxyethanol, triethylene glycol, Xanthan gum, vitamin E, B.H.T, farnesol

Principal Display Panel

NDC 70794-207-14

DermaER

Psoriasis Therapeutic ointment

Relieves and prevents skin irritation, itching, redness and flaking.

Infused vitamin E

Does not contain Steroids, Cortisone, Fragrances and Colorings

1.69 fl.oz (50 ml)

www.dermaer.com

NDC 70794-207-16

DermaER

Psoriasis Therapeutic ointment

1

Relieves and prevents

- Irritation
- Itching
- Redness
- Scaling

FDA REGISTERED

Does not contain Steroids, Cortisone, Fragrances and Colorings

2 fl.oz (59 ml)

www.DermaER.com

NDC 70794-207-17

DermaER

Psoriasis Therapeutic ointment

1

Relieves and prevents

- Irritation
- Itching
- Redness
- Scaling

FDA REGISTERED

Does not contain Steroids, Cortisone, Fragrances and Colorings

2.75 fl.oz (81 ml)

www.DermaER.com

NDC 70794-207-18

DermaER

Psoriasis Therapeutic ointment

1

Relieves and prevents

- Irritation
- Itching
- Redness
- Scaling

FDA REGISTERED

Does not contain Steroids, Cortisone, Fragrances and Colorings

3.5fl.oz (103 ml)

www.DermaER.com